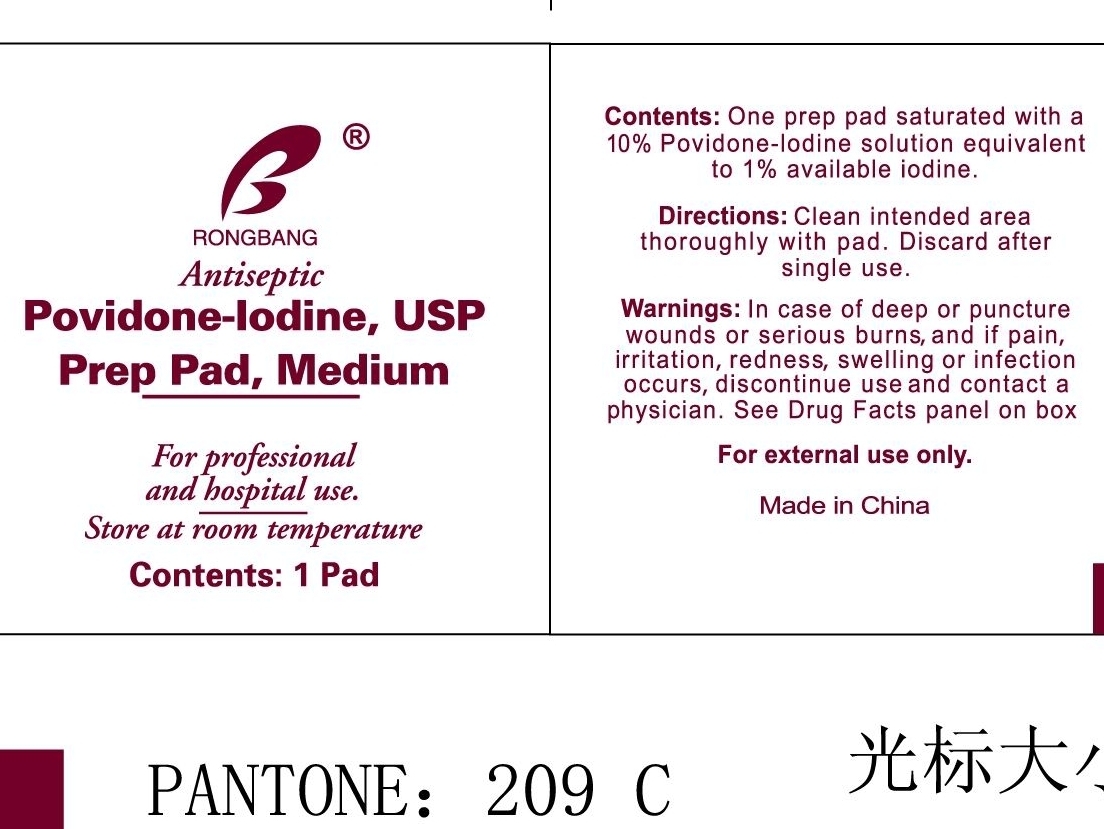 DRUG LABEL: Povidone Iodine
NDC: 49953-2805 | Form: SWAB
Manufacturer: Dalian Rongbang Medical Healthy Devices Co
Category: otc | Type: HUMAN OTC DRUG LABEL
Date: 20100702

ACTIVE INGREDIENTS: Povidone-Iodine 1 mL/10 mL
INACTIVE INGREDIENTS: water

Povidone Iodine Pad

ACTIVE INGREDIENT

10% povidone-iodine solution equivalent to 1% available iodine.

INACTIVE INGREDIENT

not listed on label

DOSAGE AND ADMINISTRATION

1 pad. for external use only

INDICATIONS AND USAGE

Clean intended area thoroughly with pad. discard after single use.

KEEP OUT OF REACH OF CHILDREN

for professional and hospital use.

WARNINGS

store at room temperature. In case of deep or puncture wounds or serious burns, and if pain, irritation, redness, swellling, or infection occurs, discontinue use and contact a physician. See drug facts panel on box. For external use only.

PURPOSE

Clean intended area.

PACKAGE LABEL

Rongbang Antiseptic, Povidone-Iodine, USP, Prep Pad, Medium